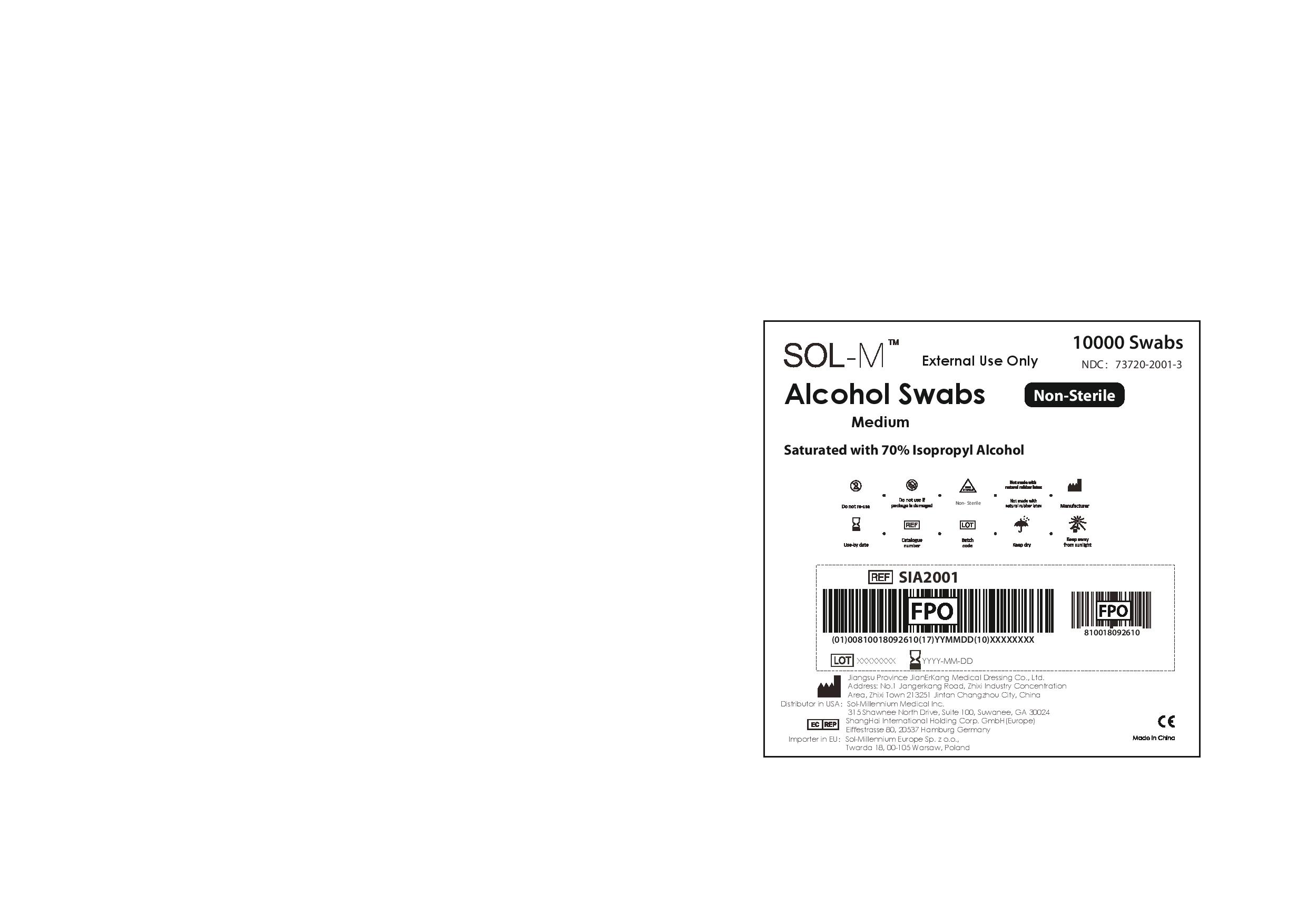 DRUG LABEL: Sol-M Alcohol Swabs Medium Non-Sterile
NDC: 73720-2001 | Form: SWAB
Manufacturer: Sol-Millennium Medical Inc
Category: otc | Type: HUMAN OTC DRUG LABEL
Date: 20220622

ACTIVE INGREDIENTS: ISOPROPYL ALCOHOL 0.7 mL/1 mL
INACTIVE INGREDIENTS: WATER

Sol-M Alcohol Swabs Medium Non-Sterile Case

Active ingredient

Isopropyl Alcohol 70%

Purpose

Isopropyl Alcohol 70%................Antiseptic Cleanser

Use

For preparation of the skin prior to an injection

Warnings

- For external use only
- Flammable, keep away from fire or flame

Do Not Use

- with electrocautery procedures
- In the eyes. If contact occurs, flush eyes with water

Stop Use

If irritation and redness develop. If condition persists consult your health care practitioner.

Keep out of reach of children

If swallowed get medical help or contact a Poison Control Center right away.

Directions

- Wipe injection site vigorously and discard

Other information

Store at room temperature 15 - 30 C (59 - 86 F)

Inactive ingredient

purified water

PACKAGE LABEL

10000 Swabs

External Use Only

NDC: 73720-2001-3

Sol-M Alcohol Swabs Non Sterile

Medium

Saturated with 70% Isopropyl Alcohol

Do not re-use

Do not use if package is damaged

Non-Sterile

Not made with natural rubber latex

Manufacturer

Use-by date

Catalogue number

Batch code

Keep dry

Keep away from sunlight

Jiangsu Province JianErKang Medical Dressing Co., Ltd.
Address: No.1 Jangerkang Road, Zhixi Industry Concentration
Area, Zhixi Town 213251 Jintan Changzhou City, China
Distributor in USA： Sol-Millennium Medical Inc.
315 Shawnee North Drive, Suite 100, Suwanee, GA 30024
ShangHai International Holding Corp. GmbH(Europe)
Eiffestrasse 80, 20537 Hamburg Germany
Importer in EU： Sol-Millennium Europe Sp. zo.o.,

Twarda 18, 00-105 Warsaw, Poland